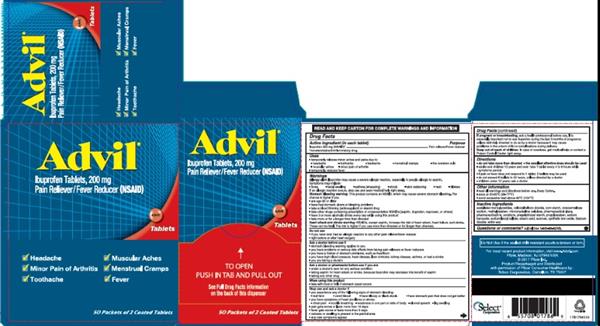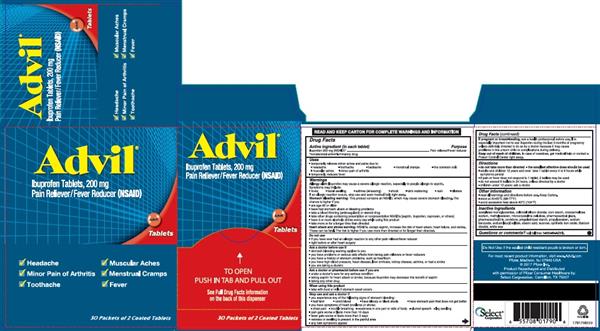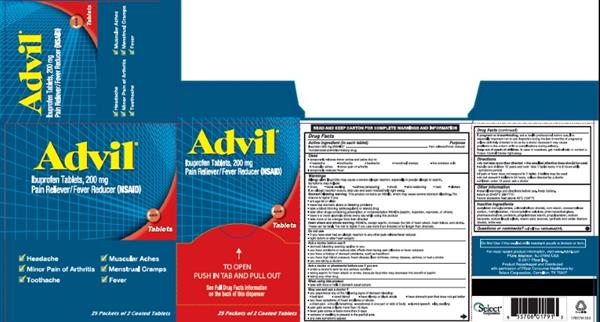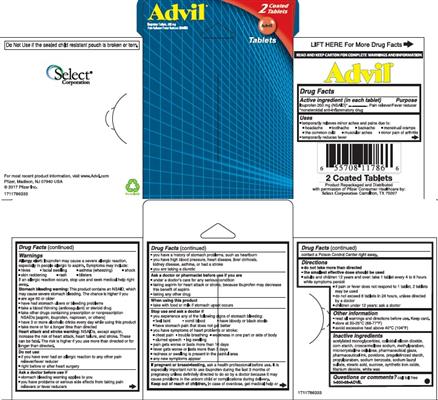 DRUG LABEL: ADVIL
NDC: 52904-791 | Form: TABLET, COATED
Manufacturer: Wyeth Pharmaceuticals Company
Category: otc | Type: HUMAN OTC DRUG LABEL
Date: 20190529

ACTIVE INGREDIENTS: IBUPROFEN 200 mg/1 1
INACTIVE INGREDIENTS: MICROCRYSTALLINE CELLULOSE; CROSCARMELLOSE SODIUM; FERRIC OXIDE RED; METHYLPARABEN; POVIDONE, UNSPECIFIED; PROPYLPARABEN; SHELLAC; SILICON DIOXIDE; SODIUM BENZOATE; SODIUM LAURYL SULFATE; STARCH, CORN; STEARIC ACID; SUCROSE; TITANIUM DIOXIDE; WHITE WAX; DIACETYLATED MONOGLYCERIDES

ADVIL Tablets
(ibuprofen)

ACTIVE INGREDIENT

Advil Tablets (in each tablet)

Ibuprofen 200 mg (NSAID)*

*nonsteroidal anti-inflammatory drug

Advil Caplets (in each caplet)

Ibuprofen 200 mg (NSAID)*

*nonsteroidal anti-inflammatory drug

Advil Gel Caplets (in each gel caplet)

Ibuprofen 200 mg (NSAID)*

*nonsteroidal anti-inflammatory drug

PURPOSE

Pain reliever/Fever reducer

USES

- temporarily relieves minor aches and pains due to:
  - headache
  - toothache
  - backache
  - menstrual cramps
  - the common cold
  - muscular aches
  - minor pain of arthritis
- temporarily reduces fever

WARNINGS

Allergy alert:

Ibuprofen may cause a severe allergic reaction, especially in people allergic to aspirin. Symptoms may include:

- hives
- facial swelling
- asthma (wheezing)
- shock
- skin reddening
- rash
- blisters

If an allergic reaction occurs, stop use and seek medical help right away.

Stomach bleeding warning:

This product contains an NSAID, which may cause severe stomach bleeding. The chance is higher if you

- are age 60 or older
- have had stomach ulcers or bleeding problems
- take a blood thinning (anticoagulant) or steroid drug
- take other drugs containing prescription or non-prescription NSAIDs [aspirin, ibuprofen, naproxen, or others]
- have 3 or more alcoholic drinks every day while using this product
- take more or for a longer time than directed

Heart attack and stroke warning

NSAIDs, except aspirin, increase the risk of heart attack, heart failure, and stroke. These can be fatal. The risk is higher if you use more than directed or for longer than directed.

Do not use

- if you have ever had an allergic reaction to any other pain reliever/fever reducer
- right before or after heart surgery

Ask a doctor before use if

- stomach bleeding warning applies to you
- you have problems or serious side effects from taking pain relievers or fever reducers
- you have a history of stomach problems, such as heartburn
- you have high blood pressure, heart disease, liver cirrhosis, kidney disease, asthma, or had a stroke
- you are taking a diuretic

Ask a doctor or pharmacist before use if you are

- under a doctor's care for any serious condition
- taking aspirin for heart attack or stroke, because ibuprofen may decrease this benefit of aspirin
- taking any other drug

When using this product

- take with food or milk if stomach upset occurs

Stop use and ask a doctor if

- you experience any of the following signs of stomach bleeding:
  - feel faint
  - vomit blood
  - have bloody or black stools
  - have stomach pain that does not get better
- you have symptoms of heart problems or stroke:
  - chest pain
  - trouble breathing
  - weakness in one part or side of body
  - slurred speech
  - leg swelling
- pain gets worse or lasts more than 10 days
- fever gets worse or lasts more than 3 days
- redness or swelling is present in the painful area
- any new symptoms appear

If pregnant or breast-feeding,

ask a health professional before use. It is especially important not to use ibuprofen during the last 3 months of pregnancy unless definitely directed to do so by a doctor because it may cause problems in the unborn child or complications during delivery.

Keep out of reach of children.

In case of overdose, get medical help or contact a Poison Control Center right away.

DIRECTIONS

Advil Tablets

- do not take more than directed
- the smallest effective dose should be used
- adults and children 12 years and over: take 1 tablet every 4 to 6 hours while symptoms persist
- if pain or fever does not respond to 1 tablet, 2 tablets may be used
- do not exceed 6 tablets in 24 hours, unless directed by a doctor
- children under 12 years: ask a doctor

Advil Caplets

- do not take more than directed
- the smallest effective dose should be used
- adults and children 12 years and over: take 1 caplet every 4 to 6 hours while symptoms persist
- if pain or fever does not respond to 1 caplet, 2 caplets may be used
- do not exceed 6 caplets in 24 hours, unless directed by a doctor
- children under 12 years: ask a doctor

Advil Gel Caplets

- do not take more than directed
- the smallest effective dose should be used
- adults and children 12 years and over: take 1 gel caplet every 4 to 6 hours while symptoms persist
- if pain or fever does not respond to 1 gel caplet, 2 gel caplets may be used
- do not exceed 6 gel caplets in 24 hours, unless directed by a doctor
- children under 12 years: ask a doctor

OTHER INFORMATION

- read all warnings and directions before use. Keep carton.
- store at 20-25°C (68-77°F)
- avoid excessive heat above 40°C (104°F)

INACTIVE INGREDIENTS

Advil Tablets

acetylated monoglycerides, colloidal silicon dioxide, corn starch, croscarmellose sodium, methylparaben, microcrystalline cellulose, pharmaceutical glaze, pharmaceutical ink, povidone, pregelatinized starch, propylparaben, sodium benzoate, sodium lauryl sulfate, stearic acid, sucrose, synthetic iron oxide, titanium dioxide, white wax

Advil Caplets

acetylated monoglycerides, colloidal silicon dioxide, corn starch, croscarmellose sodium, methylparaben, microcrystalline cellulose, pharmaceutical glaze, pharmaceutical ink, povidone, pregelatinized starch, propylparaben, sodium benzoate, sodium lauryl sulfate, stearic acid, sucrose, synthetic iron oxide, titanium dioxide, white wax

Advil Gel Caplets

colloidal silicon dioxide, corn starch, croscarmellose sodium, FD&C red no. 40, FD&C yellow no. 6, fractionated coconut oil, gelatin, glycerin, hypromellose, pharmaceutical ink, pregelatinized starch, propyl gallate, purified water, sodium lauryl sulfate, stearic acid, synthetic iron oxides, titanium dioxide, triacetin

Questions or comments?

call toll free 1-800-88-ADVIL

HOW SUPPLIED

Product: 52904-794

NDC: 52904-794-05 2 TABLET, COATED in a POUCH / 1 in a CARTON

NDC: 52904-794-01 2 TABLET, COATED in a POUCH / 1 in a BLISTER PACK

NDC: 52904-794-02 2 TABLET, COATED in a POUCH / 2 in a BLISTER PACK

NDC: 52904-794-06 2 TABLET, COATED in a POUCH / 2 in a CARTON

Product: 52904-786

NDC: 52904-786-50 2 TABLET, COATED in a POUCH / 50 in a CASE

Product: 52904-790

NDC: 52904-790-30 2 TABLET, COATED in a POUCH / 30 in a CASE

Product: 52904-791

NDC: 52904-791-25 2 TABLET, COATED in a POUCH / 25 in a CASE